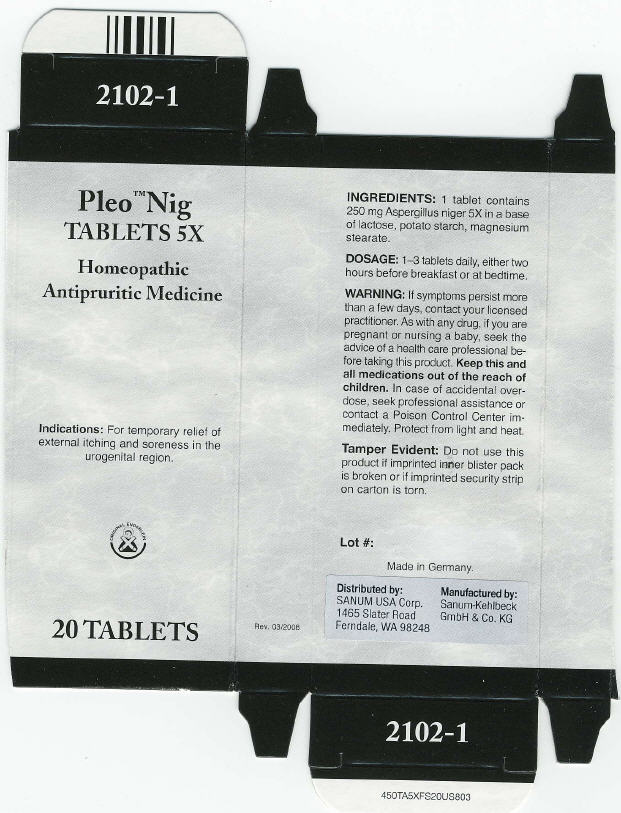 DRUG LABEL: Pleo Nig
NDC: 60681-2102 | Form: TABLET
Manufacturer: Sanum Kehlbeck GmbH & Co. KG
Category: homeopathic | Type: HUMAN OTC DRUG LABEL
Date: 20091012

ACTIVE INGREDIENTS: aspergillus niger var. niger 5 [HP_X]/1 1
INACTIVE INGREDIENTS: lactose; Starch, Potato; Magnesium Stearate

Pleo™ Nig
TABLETS 5X

Homeopathic Antipruritic Medicine

20 TABLETS

Indications

For temporary relief of external itching and soreness in the urogenital region.

INGREDIENTS

1 tablet contains 250 mg Aspergillus niger 5X in a base of lactose, potato starch, magnesium stearate.

DOSAGE

1–3 tablets daily, either two hours before breakfast or at bedtime.

WARNING

If symptoms persist more than a few days, contact your licensed practitioner. As with any drug, if you are pregnant or nursing a baby, seek the advice of a health care professional before taking this product.

KEEP OUT OF REACH OF CHILDREN

Keep this and all medications out of the reach of children. In case of accidental overdose, seek professional assistance or contact a Poison Control Center immediately.

STORAGE AND HANDLING

Protect from light and heat.

Tamper Evident

Do not use this product if imprinted inner blister pack is broken or if imprinted security strip on carton is torn.

Lot #:

Made in Germany.

Distributed by:
SANUM USA Corp.
1465 Slater Road
Ferndale, WA 98248

Manufactured by:
Sanum-Kehlbeck
GmbH & Co. KG

Rev. 03/2008

PRINCIPAL DISPLAY PANEL - 20 Tablets Carton

Pleo™ Nig
TABLETS 5X

Homeopathic
Antipruritic Medicine

lndications: For temporary relief of
external itching and soreness in the
urogenital region.

ORIGINAL ENDERLEIN

20 TABLETS